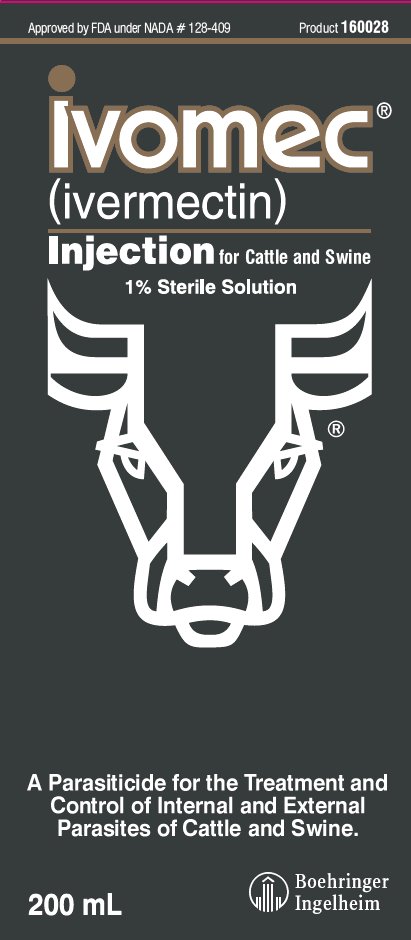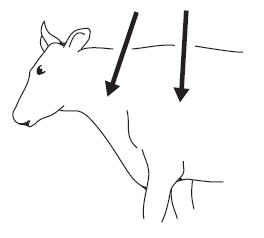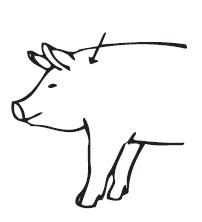 DRUG LABEL: IVOMEC
NDC: 0010-4743 | Form: INJECTION, SOLUTION
Manufacturer: Boehringer Ingelheim Animal Health USA Inc
Category: animal | Type: OTC ANIMAL DRUG LABEL
Date: 20240625

ACTIVE INGREDIENTS: ivermectin 10 mg/1 mL
INACTIVE INGREDIENTS: GLYCEROL FORMAL 0.4 mL/1 mL; PROPYLENE GLYCOL

Ivomec®
(ivermectin)
Injection for Cattle and Swine

Approved by FDA under NADA # 128-409

1% Sterile Solution

A Parasiticide for the Treatment and Control of Internal and External Parasites of Cattle and Swine

Consult your veterinarian for assistance in the diagnosis, treatment and control of parasitism.

INTRODUCTION

IVOMEC® (ivermectin) is an injectable parasiticide for cattle and swine. One low-volume dose effectively treats and controls the following internal and external parasites that may impair the health of cattle and swine: gastrointestinal roundworms (including inhibited Ostertagia ostertagi in cattle), lungworms, grubs, sucking lice, and mange mites of cattle; and gastrointestinal roundworms, lungworms, lice, and mange mites of swine. Discovered and developed by scientists from Merck Research Laboratories, ivermectin is a novel chemical entity. Its convenience, broad-spectrum efficacy, and safety margin make IVOMEC Injection a unique product for parasite control of cattle and swine.

PRODUCT DESCRIPTION

Ivermectin is derived from the avermectins, a family of potent, broad-spectrum antiparasitic agents isolated from fermentation of Streptomyces avermitilis.

IVOMEC Injection is a clear, ready-to-use, sterile solution containing 1% ivermectin, 40% glycerol formal, and propylene glycol, q.s. ad 100%. IVOMEC Injection is formulated to deliver the recommended dose level of 200 mcg ivermectin/kilogram of body weight in cattle when given subcutaneously at the rate of 1 mL/110 lb (50 kg). In Swine, IVOMEC Injection is formulated to deliver the recommended dose level of 300 mcg ivermectin/kilogram body weight when given subcutaneously in the neck at the rate of 1 mL per 75 lb (33 kg).

MODE OF ACTION

Ivermectin is a member of the macrocyclic lactone class of endectocides which have a unique mode of action. Compounds of the class bind selectively and with high affinity to glutamate-gated chloride ion channels which occur in invertebrate nerve and muscle cells. This leads to an increase in the permeability of the cell membrane to chloride ions with hyperpolarization of the nerve or muscle cell, resulting in paralysis and death of the parasite. Compounds of this class may also interact with other ligand-gated chloride channels, such as those gated by the neurotransmitter gamma-aminobutyric acid (GABA).

The margin of safety for compounds of this class is attributable to the fact that mammals do not have glutamate-gated chloride channels, the macrocyclic lactones have a low affinity for other mammalian ligandgated chloride channels and they do not readily cross the blood-brain barrier.

INDICATIONS

Cattle: IVOMEC Injection is indicated for the effective treatment and control of the following harmful species of gastrointestinal roundworms, lungworms, grubs, sucking lice, and mange mites in cattle:

Gastrointestinal Roundworms (adults and fourth-stage larvae): Ostertagia ostertagi (including inhibited O. ostertagi), O. lyrata, Haemonchus placei, Trichostrongylus axei, T. colubriformis, Cooperia oncophora, C. punctata, C. pectinate, Oesophagostomum radiatum, Bunostomum phlebotomum, Nematodirus helvetianus (adults only), N. spathiger (adults only)

Lungworms (adults and fourth-stage larvae): Dictyocaulus viviparus

Cattle Grubs (parasitic stages): Hypoderma bovis, H. lineatum

Sucking Lice: Linognathus vituli, Haematopinus eurysternus, Solenopotes capillatus

Mites (scabies): Psoroptes ovis (syn. P. communis var. bovis), Sarcoptes scabiei var. bovis

Persistent Activity

IVOMEC Injection has been proved to effectively control infections and to protect cattle from reinfection with Dictyocaulus viviparus and Oesophagostomum radiatum for 28 days after treatment; Ostertagia ostertagi, Trichostrongylus axei and Cooperia punctata for 21 days after treatment; Haemonchus placei and Cooperia oncophora for 14 days after treatment.

Swine: IVOMEC Injection is indicated for the effective treatment and control of the following harmful species of gastrointestinal roundworms, lungworms, lice, and mange mites in swine:

Gastrointestinal Roundworms: Large roundworm, Ascaris suum (adults and fourth-stage larvae), Red stomach worm, Hyostrongylus rubidus (adults and fourth-stage larvae), Nodular worm, Oesophagostomum spp. (adults and fourth-stage larvae), Threadworm, Strongyloides ransomi (adults)

Somatic Roundworm Larvae: Threadworm, Strongyloides ransomi (somatic larvae)

Sows must be treated at least seven days before farrowing to prevent infection in piglets.

Lungworms: Metastrongylus spp. (adults)

Lice: Haematopinus suis

Mange Mites: Sarcoptes scabiei var. suis

DOSAGE

Cattle: IVOMEC Injection should be given only by subcutaneous injection under the loose skin in front of or behind the shoulder at the recommended dose level of 200 mcg of ivermectin per kilogram of body weight. Each mL of IVOMEC contains 10 mg of ivermectin, sufficient to treat 110 lb (50 kg) of body weight (maximum 10 mL per injection site).

Body Weight (lb) | Dose Volume (mL)
220 | 2
330 | 3
440 | 4
550 | 5
660 | 6
770 | 7
880 | 8
990 | 9
1100 | 10

Swine: IVOMEC Injection should be given only by subcutaneous injection in the neck of swine at the recommended dose level of 300 mcg of ivermectin per kilogram (2.2 lb) of body weight. Each mL of IVOMEC contains 10 mg of ivermectin, sufficient to treat 75 lb of body weight.

 | Body Weight (lb) | Dose Volume (mL)
Growing Pigs | 19 | 1/4
 | 38 | 1/2
 | 75 | 1
 | 150 | 2
Breeding Animals | 225 | 3
(Sows, Gilts, and Boars) | 300 | 4
 | 375 | 5
 | 450 | 6

Do not underdose. Ensure each animal receives a complete dose based on a current body weight. Underdosing may result in ineffective treatment, and encourage the development of parasite resistance.

ADMINISTRATION

Any single-dose syringe or standard automatic syringe equipment may be used with the 50 mL bottle. Use the 50 mL bottle within 6 months of first puncture and puncture a maximum of 12 times. If more than 12 punctures are anticipated, the use of multi-dosing equipment is recommended. When using a draw-off spike or needle with bore diameter larger than 16-gauge, discard any product remaining in the bottle immediately after use. When using the 200 mL, 500 mL or 1000 mL pack size, use only automatic syringe equipment. Discard any product remaining in the pack immediately after use.

Use sterile equipment and sanitize the injection site by applying a suitable disinfectant. Clean, properly disinfected needles should be used to reduce the potential for injection site infections. The rubber stopper should also be disinfected with alcohol to prevent contamination of the contents. No special handling or protective clothing is necessary.

Cattle: IVOMEC (ivermectin) Injection is to be given subcutaneously only, to reduce risk of potentially fatal clostridial infection of the injection site. Animals should be appropriately restrained to achieve the proper route of administration. Use of a 16-gauge, 1/2 to 3/4" needle is suggested. Inject under the loose skin in front of or behind the shoulder (see illustration).

Swine: IVOMEC Injection is to be given subcutaneously in the neck. Animals should be appropriately restrained to achieve the proper route of administration. Use of a 16- or 18-gauge needle is suggested for sows and boars, while an 18- or 20-gauge needle may be appropriate for young animals. Inject under the skin, immediately behind the ear (see illustration). Mild and transient pain reactions may be seen in some swine following subcutaneous administration.

Recommended Treatment Program

Swine: At the time of initiating any parasite control program, it is important to treat all breeding animals in the herd. After the initial treatment, use IVOMEC Injection regularly as follows:

BREEDING ANIMALS

Sows: Treat prior to farrowing, preferably 7–14 days before, to minimize infection of piglets.

Gilts: Treat 7–14 days prior to breeding.

Treat 7–14 days prior to farrowing.

Boars: Frequency and need for treatments are dependent upon exposure. Treat at least two times a year.

FEEDER PIGS

(Weaners/Growers/Finishers)

All weaner/feeder pigs should be treated before placement in clean quarters.

Pigs exposed to contaminated soil or pasture may need retreatment if reinfection occurs.

NOTE:

(1) IVOMEC Injection has a persistent drug level sufficient to control mite infestations throughout the egg to adult life cycle. However, since the ivermectin effect is not immediate, care must be taken to prevent reinfestation from exposure to untreated animals or contaminated facilities. Generally, pigs should not be moved to clean quarters or exposed to uninfested pigs for approximately one week after treatment. Sows should be treated at least one week before farrowing to minimize transfer of mites to newborn baby pigs.
(2) Louse eggs are unaffected by IVOMEC Injection and may require up to three weeks to hatch. Louse infestations developing from hatching eggs may require retreatment.
(3) Consult a veterinarian for aid in the diagnosis and control of internal and external parasites of swine.

Special Minor Use

Reindeer: For the treatment and control of warbles (Oedemagena tarandi) in reindeer, inject 200 micrograms ivermectin per kilogram of body weight, subcutaneously. Follow use directions for cattle as described under ADMINISTRATION.

American Bison: For the treatment and control of grubs (Hypoderma bovis) in American bison, inject 200 micrograms ivermectin per kilogram of body weight, subcutaneously. Follow use directions for cattle as described under ADMINISTRATION.

RESIDUE WARNING

Do not treat reindeer or American bison within 8 weeks (56 days) of slaughter.

WARNING

NOT FOR USE IN HUMANS.

Keep this and all drugs out of the reach of children.

The Safety Data Sheet (SDS) contains more detailed occupational safety information. To report suspected adverse drug events, for technical assistance, or to obtain a copy of the SDS, contact Boehringer Ingelheim Animal Health USA Inc. at 1-888-637-4251. For additional information about adverse drug experience reporting for animal drugs, contact FDA at 1-888-FDA-VETS, or at www.fda.gov/reportanimalae.

RESIDUE WARNING

Do not treat cattle within 35 days of slaughter. Because a withdrawal time in milk has not been established, do not use in female dairy cattle of breeding age. A withdrawal period has not been established for this product in pre-ruminating calves. Do not use in calves to be processed for veal. Do not treat swine within 18 days of slaughter.

PRECAUTIONS

Transitory discomfort has been observed in some cattle following subcutaneous administration. A low incidence of soft tissue swelling at the injection site has been observed. These reactions have disappeared without treatment. For cattle, divide doses greater than 10 mL between two injection sites to reduce occasional discomfort or site reaction. Use sterile equipment and sanitize the injection site by applying a suitable disinfectant. Clean, properly disinfected needles should be used to reduce the potential for injection site infections.

Observe cattle for injection site reactions. Reactions may be due to clostridial infection and should be aggressively treated with appropriate antibiotics. If injection site infections are suspected, consult your veterinarian.

This product is not for intravenous or intramuscular use.

IVOMEC Injection for Cattle and Swine has been developed specifically for use in cattle, swine, reindeer, and American bison only. This product should not be used in other animal species as severe adverse reactions, including fatalities in dogs, may result.

Restricted Drug (California) - use only as directed.

When to Treat Cattle with Grubs

IVOMEC effectively controls all stages of cattle grubs. However, proper timing of treatment is important. For most effective results, cattle should be treated as soon as possible after the end of the heel fly (warble fly) season. Destruction of Hypoderma larvae (cattle grubs) at the period when these grubs are in vital areas may cause undesirable host-parasite reactions including the possibility of fatalities. Killing Hypoderma lineatum when it is in the tissue surrounding the esophagus (gullet) may cause salivation and bloat; killing H. bovis when it is in the vertebral canal may cause staggering or paralysis. These reactions are not specific to treatment with IVOMEC, but can occur with any successful treatment of grubs. Cattle should be treated either before or after these stages of grub development. Consult your veterinarian concerning the proper time for treatment. Cattle treated with IVOMEC after the end of the heel fly season may be retreated with IVOMEC during the winter for internal parasites, mange mites, or sucking lice without danger of grub-related reactions. A planned parasite control program is recommended.

OTHER WARNINGS

Parasite resistance may develop to any dewormer, and has been reported for most classes of dewormers.

Treatment with a dewormer used in conjunction with parasite management practices appropriate to the geographic area and the animal(s) to be treated may slow the development of parasite resistance.

Fecal examinations or other diagnostic tests and parasite management history should be used to determine if the product is appropriate for the herd, prior to the use of any dewormer. Following the use of any dewormer, effectiveness of treatment should be monitored (for example, with the use of a fecal egg count reduction test or another appropriate method).

A decrease in a drug's effectiveness over time as calculated by fecal egg count reduction tests may indicate the development of resistance to the dewormer administered. Your parasite management plan should be adjusted accordingly based on regular monitoring.

Environmental Safety

Studies indicate that when ivermectin comes in contact with soil, it readily and tightly binds to the soil and becomes inactive over time. Free ivermectin may adversely affect fish and certain aquatic organisms. Do not permit water runoff from feed lots to enter lakes, streams or ponds. Do not contaminate water by direct application or by improper disposal of drug containers. Dispose of containers in an approved landfill or by incineration.

As with other avermectins, ivermectin is excreted in the dung of treated animals and can inhibit the reproduction and growth of pest and beneficial insects that use dung as a source of food and for reproduction. The magnitude and duration of such effects are species and life-cycle specific. When used according to label directions, the product is not expected to have an adverse impact on populations of dung-dependent insects.

STORAGE CONDITIONS

Store at or below 25°C (77°F) with excursions permitted up to 30°C (86°F). Protect product from light.

HOW SUPPLIED

IVOMEC Injection for Cattle and Swine is available in four ready-to-use pack sizes:

The 50 mL pack is a multiple-dose, rubber-capped bottle. Each bottle contains sufficient solution to treat 10 head of 550 lb (250 kg) cattle or 100 head of 38 lb (17.3 kg) swine.

The 200 mL pack is a soft, collapsible pack designed for use with automatic syringe equipment. Each pack contains sufficient solution to treat 40 head of 550 lb (250 kg) cattle or 400 head of 38 lb (17.3 kg) swine.

The 500 mL pack is a soft, collapsible pack designed for use with automatic syringe equipment. Each pack contains sufficient solution to treat 100 head of 550 lb (250 kg) cattle or 1000 head of 38 lb (17.3 kg) swine.

The 1000 mL is a soft, collapsible pack designed for use with automatic syringe equipment. Each pack contains sufficient solution to treat 200 head of 550 lb (250 kg) cattle or 2000 head of 38 lb (17.3 kg) swine.

IVOMEC®, Cattle Head Logo and Pig Head Logo are registered trademarks of Boehringer Ingelheim Animal Health USA Inc.

©2023 Boehringer Ingelheim Animal Health USA Inc. All rights reserved.

Marketed by:
Boehringer Ingelheim Animal Health USA Inc.
Duluth, GA 30096

Rev. 08/2023 4033932

609077-001